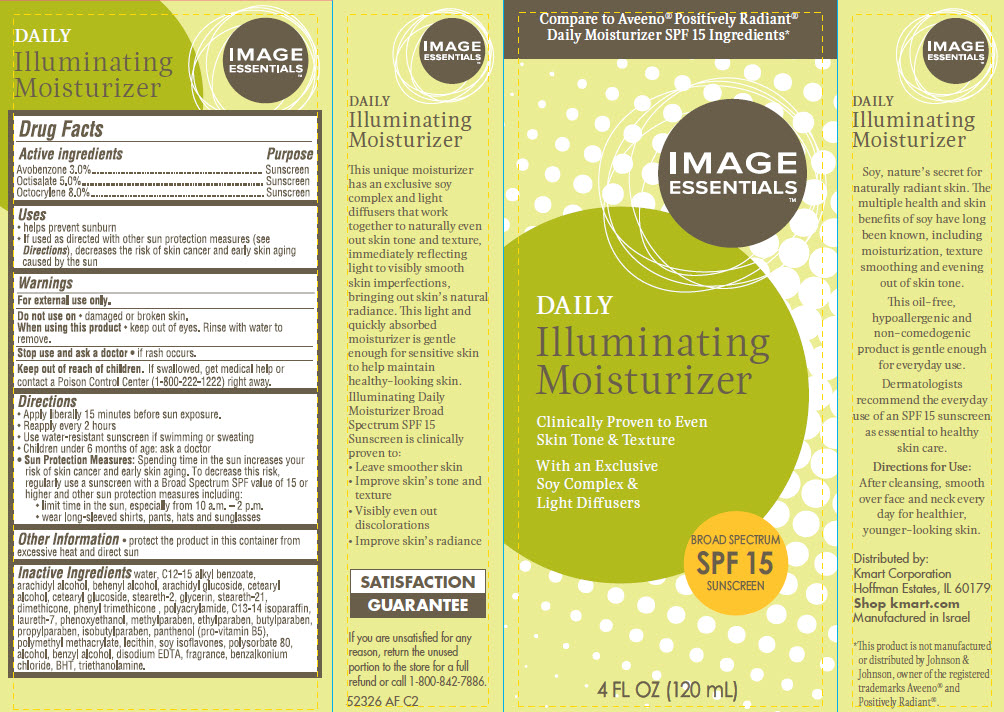 DRUG LABEL: Image Essentials Daily Illuminating Moisturizer Broad Spectrum SPF 15 Sunscreen
NDC: 49738-746 | Form: CREAM
Manufacturer: KMART Corporation
Category: otc | Type: HUMAN OTC DRUG LABEL
Date: 20140922

ACTIVE INGREDIENTS: AVOBENZONE 3 g/100 g; OCTISALATE 5 g/100 g; OCTOCRYLENE 8 g/100 g
INACTIVE INGREDIENTS: WATER; ALKYL (C12-15) BENZOATE; ARACHIDYL ALCOHOL; DOCOSANOL; ARACHIDYL GLUCOSIDE; CETOSTEARYL ALCOHOL; CETEARYL GLUCOSIDE; STEARETH-2; GLYCERIN; STEARETH-21; DIMETHICONE; PHENYL TRIMETHICONE; C13-14 ISOPARAFFIN; LAURETH-7; PHENOXYETHANOL; METHYLPARABEN; ETHYLPARABEN; BUTYLPARABEN; PROPYLPARABEN; ISOBUTYLPARABEN; PANTHENOL; POLY(METHYL METHACRYLATE; 450000 MW); SOY ISOFLAVONES; POLYSORBATE 80; ALCOHOL; BENZYL ALCOHOL; EDETATE DISODIUM; BENZALKONIUM CHLORIDE; BUTYLATED HYDROXYTOLUENE; TROLAMINE

Image Essentials™ Daily Illuminating Moisturizer

Active ingredient

Avobenzone 3.0%

Octisalate 5.0%

Octocrylene 8.0%

Purpose

Sunscreen

Uses

- helps prevent sunburn
- If used as directed with other sun protection measures (see Directions), decreases the risk of skin cancer and early skin aging caused by the sun

Warnings

For external use only.

Do not use on

- damaged or broken skin.

When using this product

- keep out of eyes. Rinse with water to remove.

Stop use and ask a doctor

- if rash occurs.

Keep Out of Reach of Children.

If swallowed, get medical help or contact a Poison Control Center (1-800-222-1222) right away.

Directions

- Apply liberally 15 minutes before sun exposure.
- Reapply every 2 hours
- Use water-resistant sunscreen if swimming or sweating
- Children under 6 months of age: ask a doctor
- Sun Protection Measures: Spending time in the sun increases your risk of skin cancer and early skin aging. To decrease this risk, regularly use a sunscreen with a Broad Spectrum SPF value of 15 or higher and other sun protection measures including:
  1. limit time in the sun, especially from 10 a.m. - 2 p.m.
  2. wear long-sleeved shirts, pants, hats and sunglasses

Other Information

- protect the product in this container from excessive heat and direct sun

Inactive Ingredients

water, C12-15 alkyl benzoate, arachidyl alcohol, beheynl alcohol, arachidyl glucoside, cetearyl alcohol, cetearyl glucoside, steareth-2, glycerin, steareth-21, dimethicone, phenyl trimethicone, polyacrylamide, C13-14 isoparaffin, laureth-7, phenoxyethanol, methylparaben, ethylparaben, butylparaben, propylparaben, isobutylparaben, panthenol (pro-vitamin B5), polymethyl methacrylate, lecithin, soy isoflavones, polysorbate 80, alcohol, benzyl alcohol, disodium EDTA, fragrance, benzalkonium chloride, BHT, triethanolamine.

Package/Label Principal Display Panel

Compare to Aveeno® Positively Radiant® Daily Moisturizer SPF 15 Ingredients*

IMAGE
ESSENTIALS™

DAILY
Illuminating
Moisturizer

Clinically Proven to Even
Skin Tone & Texture

With an Exclusive
Soy Complex &
Light Diffusers

BROAD SPECTRUM
SPF 15
SUNSCREEN

4 FL OZ (120 mL)

IMAGE
ESSENTIALS™

DAILY
Illuminating
Moisturizer

This unique moisturizer has an exclusive soy complex and light diffusers that work together to naturally even out skin tone and texture, immediately reflecting light to visibly smooth skin imperfections, bringing out skin’s natural radiance. This light and quickly absorbed moisturizer is gentle enough for sensitive skin to help maintain healthy-looking skin.

Illuminating Daily Moisturizer Broad Spectrum SPF 15 Sunscreen is clinically proven to:

- Leave smoother skin
- Improve skin’s tone and texture
- Visibly even out discolorations
- Improve skin’s radiance

SATISFACTION
GUARANTEE

If you are unsatisfied for any reason, return the unused portion to the store for a full refund or call 1-800-842-7886.

52326 AF C2

IMAGE
ESSENTIALS™

DAILY
Illuminating
Moisturizer

Soy, nature’s secret for naturally radiant skin. The multiple health and skin benefits of soy have long been known, including moisturization, texture smoothing and evening out of skin tone.

This oil-free, hypoallergenic and non-comedogenic product is gentle enough for everyday use.

Dermatologists recommend the everyday use of an SPF 15 sunscreen as essential to healthy skin care.

Directions for Use:

After cleansing, smooth over face and neck every day for healthier, younger-looking skin.

Distributed by:
Kmart Corporation
Hoffman Estates, IL 60179
Shop kmart.com
Manufactured in Israel

*This product is not manufactured or distributed by Johnson & Johnson, owner of the registered trademarks Aveeno® and Positively Radiant®.

Carton Label